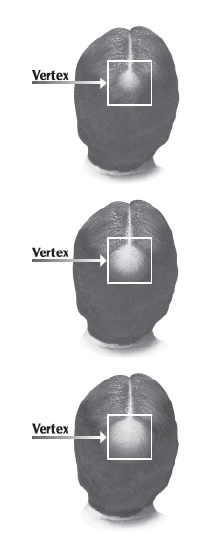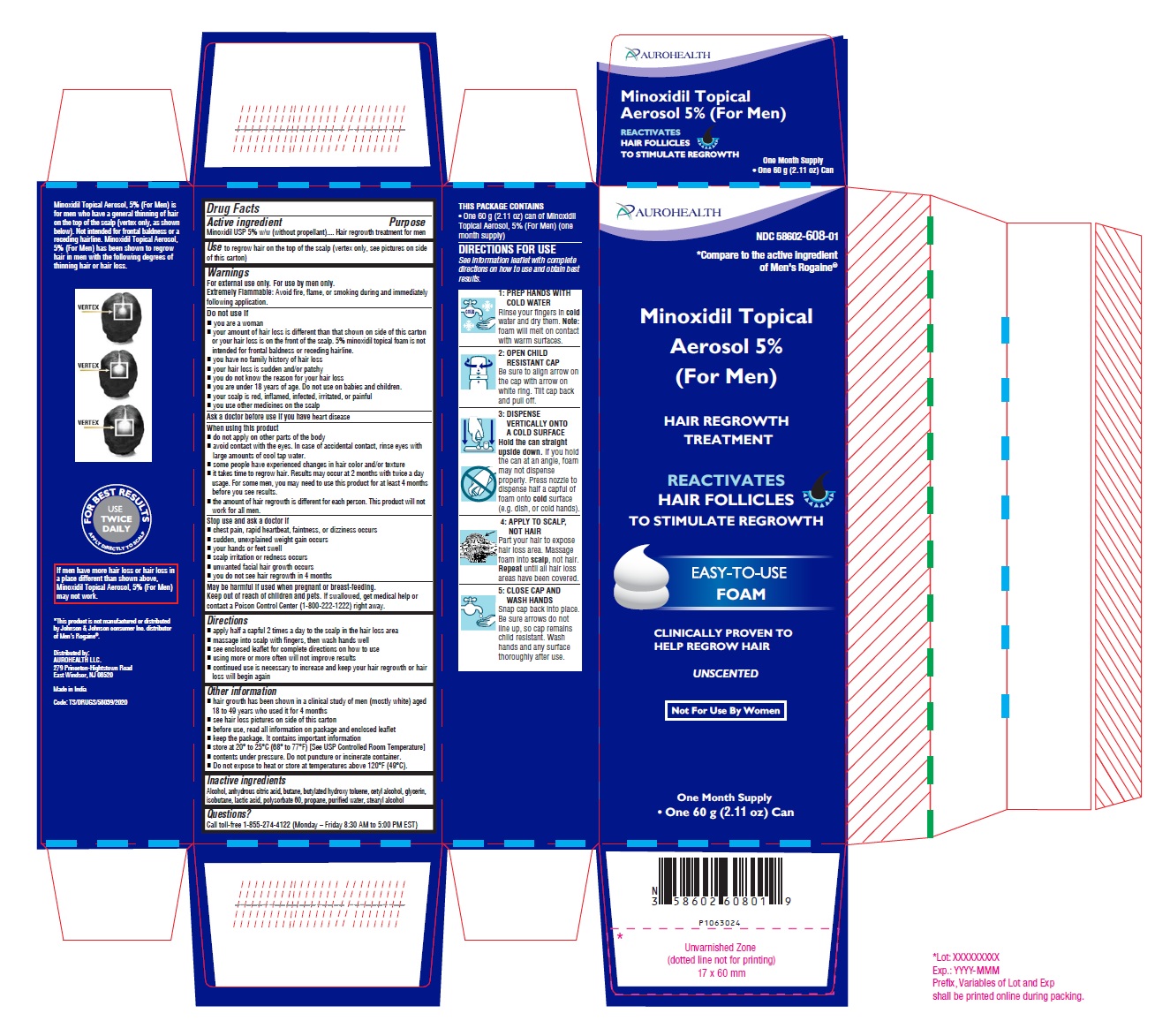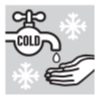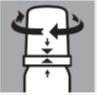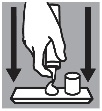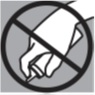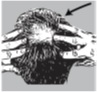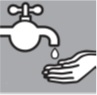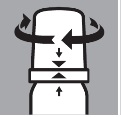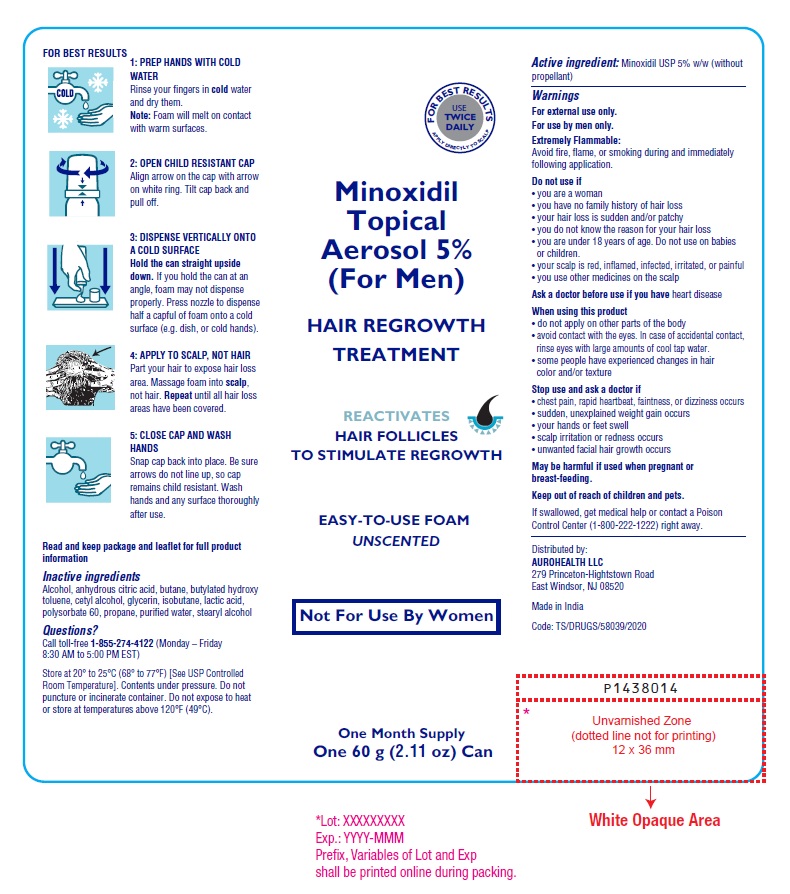 DRUG LABEL: MINOXIDIL 5% (FOR MEN)
NDC: 58602-608 | Form: AEROSOL, FOAM
Manufacturer: Aurohealth LLC
Category: otc | Type: Human OTC Drug Label
Date: 20260122

ACTIVE INGREDIENTS: MINOXIDIL 50 mg/1 g
INACTIVE INGREDIENTS: ALCOHOL; ANHYDROUS CITRIC ACID; BUTANE; BUTYLATED HYDROXYTOLUENE; CETYL ALCOHOL; GLYCERIN; ISOBUTANE; LACTIC ACID, UNSPECIFIED FORM; POLYSORBATE 60; PROPANE; WATER; STEARYL ALCOHOL

Active ingredient

Minoxidil USP 5% w/w (without propellant)

Purpose

Hair regrowth treatment for men

Use

to regrow hair on the top of the scalp (vertex only, see pictures on side of this carton)

Warnings

For external use only. For use by men only.
Extremely Flammable:
Avoid fire, flame, or smoking during and immediately following application.

Do not use if

- you are a woman
- your amount of hair loss is different than that shown on side of this carton or your hair loss is on the front of the scalp. 5% minoxidil topical foam is not intended for frontal baldness or receding hairline.
- you have no family history of hair loss
- your hair loss is sudden and/or patchy
- you do not know the reason for your hair loss
- you are under 18 years of age. Do not use on babies and children.
- your scalp is red, inflamed, infected, irritated, or painful
- you use other medicines on the scalp

Ask a doctor before use if you have

heart disease

When using this product

- do not apply on other parts of the body
- avoid contact with the eyes. In case of accidental contact, rinse eyes with large amounts of cool tap water.
- some people have experienced changes in hair color and/or texture
- it takes time to regrow hair. Results may occur at 2 months with twice a day usage. For some men, you may need to use this product for at least 4 months before you see results.
- the amount of hair regrowth is different for each person. This product will not work for all men.

Stop use and ask a doctor if

- chest pain, rapid heartbeat, faintness, or dizziness occurs
- sudden, unexplained weight gain occurs
- your hands or feet swell
- scalp irritation or redness occurs
- unwanted facial hair growth occurs
- you do not see hair regrowth in 4 months

PREGNANCY OR BREAST FEEDING

May be harmful if used when pregnant or breast-feeding.

Keep out of reach of children and pets. If swallowed, get medical help or contact a Poison Control Center (1-800-222-1222) right away.

Directions

- apply half a capful 2 times a day to the scalp in the hair loss area
- massage into scalp with fingers, then wash hands well
- see enclosed leaflet for complete directions on how to use
- using more or more often will not improve results
- continued use is necessary to increase and keep your hair regrowth or hair loss will begin again

Other information

- hair growth has been shown in a clinical study of men (mostly white) aged 18 to 49 years who used it for 4 months
- see hair loss pictures on side of this carton
- before use, read all information on package and enclosed leaflet
- keep the package. It contains important information
- store at 20° to 25°C (68° to 77°F) [See USP Controlled Room Temperature]
- contents under pressure. Do not puncture or incinerate container.
- Do not expose to heat or store at temperatures above 120°F (49°C).

Inactive ingredients

Alcohol, anhydrous citric acid, butane, butylated hydroxy toluene, cetyl alcohol, glycerin, isobutane, lactic acid, polysorbate 60, propane, purified water, stearyl alcohol

Questions?

Call toll-free 1-855-274-4122 (Monday – Friday 8:30 AM to 5:00 PM EST)
Distributed by:
AUROHEALTH LLC.
279 Princeton-Hightstown Road
East Windsor, NJ 08520
Made in India
Code: TS/DRUGS/58039/2020

IMPORTANT INFORMATION ABOUT

Minoxidil Topical Aerosol 5% (For Men)

HAIR REGROWTH TREATMENT

REACTIVATES

HAIR FOLLICLES TO STIMULATE REGROWTH

EASY-TO-USE

FOAM

CLINICALLY PROVEN TO HELP REGROW HAIR

UNSCENTED

Not For Use By Women

Minoxidil Topical Aerosol 5% (For Men)

HAIR REGROWTH TREATMENT

Save leaflet for future reference

- It takes time to regrow hair. Results may occur at 2 months with twice a day usage. For some men, you may need to use this product for at least 4 months before you see results.

Please read this leaflet carefully. It will help you understand how to use Minoxidil Topical Aerosol 5% (Foam) and what to expect from its use. If you have any questions after reading this leaflet, or anytime while using Minoxidil Topical Aerosol 5% (Foam), you should ask your health care professional or call us at 1-855-274-4122 (Monday – Friday 8:30 AM to 5:00 PM EST).

What is Men's Minoxidil Topical Aerosol 5% (Foam)?

Minoxidil Topical Aerosol 5% (Foam) is a white foam containing 5% minoxidil for use only on the scalp to help regrow hair in men.

Who may use Men's Minoxidil Topical Aerosol 5% (Foam)?

Minoxidil Topical Aerosol 5% (Foam) is for use only by men. Minoxidil Topical Aerosol 5% (Foam) may be appropriate for you if you are a male at least 18 years old and experiencing gradually thinning hair or gradual hair loss on the top of the scalp (vertex only, as shown below). It is not intended for frontal baldness or a receding hairline. The common inherited thinning or hair loss process begins slowly and may become noticeable only after years of gradual loss.

Minoxidil Topical Aerosol 5% (Foam) is for men with hair loss or thinning hair that begins on the vertex of the scalp. Minoxidil Topical Aerosol 5% (Foam) is more likely to regrow hair in men with hair loss in the range shown below. If men have more hair loss than shown, Minoxidil Topical Aerosol 5% (Foam) may not work.

Many of those experiencing hair loss have other family members with gradually thinning hair or hair loss. If you have no family history of gradually thinning hair or of gradual hair loss, or your hair loss is patchy, see your doctor.

Who should NOT use Men's Minoxidil Topical Aerosol 5% (Foam)?

- Women should not use Men's Minoxidil Topical Aerosol 5% (Foam).
- Minoxidil Topical Aerosol 5% (Foam) should not be used on babies or children under 18 years old.
- Minoxidil Topical Aerosol 5% (Foam) will not prevent or improve hair loss which may occur with the use of some prescription and non-prescription medications, certain severe nutritional problems (very low body iron; too much vitamin A intake), low thyroid states (hypothyroidism), chemotherapy, or diseases which cause scarring of the scalp.

Also, Minoxidil Topical Aerosol 5% (Foam) will not improve hair loss due to:

- damage from the use of hair care products which cause scarring or deep burns of the scalp.
- hair grooming methods such as cornrowing or ponytails which require pulling the hair tightly back from the scalp.

Do not use if you are not sure of the reason for your hair loss.

Will Men's Minoxidil Topical Aerosol 5% (Foam) work for me?

The amount of hair regrowth is different for each person. Not everyone will respond to Minoxidil Topical Aerosol 5% (Foam). The response to Men's Minoxidil Topical Aerosol 5% (Foam) cannot be predicted. It is unlikely anyone will be able to grow back all their hair.

However, to see your best results with Men's Minoxidil Topical Aerosol 5% (Foam), make sure you get the medicine directly to the scalp and apply it twice a day, every day.

You may get better results if you have been losing your hair for a short period of time or have little hair loss. However, for some men Minoxidil Topical Aerosol 5% (Foam) may not work.

How soon can I expect results from using Men's Minoxidil Topical Aerosol 5% (Foam)?

Since normal hair usually grows only 1/2 to 1 inch per month, hair regrowth with Minoxidil Topical Aerosol 5% (Foam) also takes time.

Results may be seen as early as 2 months with twice daily use. For some men, it may take at least 4 months for results to be seen. If you do not see any results after 4 months, stop using Minoxidil Topical Aerosol 5% (Foam) and seek the advice of your physician.

When you first begin to use Minoxidil Topical Aerosol 5% (Foam), your hair loss may increase temporarily for up to 2 weeks. This is likely a sign that you are getting rid of old hairs in order to regrow more new hairs. This temporary increase in hair loss is expected and is part of the process for how Minoxidil Topical Aerosol 5% (Foam) regrows hair. Remember, this increased hair loss is temporary. However, if it continues after two weeks, see your physician.

If Men's Minoxidil Topical Aerosol 5% (Foam) is working, what will the hair look like?

At first, hair growth is usually soft, downy, colorless hairs (like peach fuzz). After further use, the new hairs should be the same color and thickness as the other hairs on your scalp.

How long do I need to use Men's Minoxidil Topical Aerosol 5% (Foam)?

If you experience hair regrowth, continued use of Minoxidil Topical Aerosol 5% (Foam) is necessary or the hair loss will begin again.

What happens if I completely stop using Men's Minoxidil Topical Aerosol 5% (Foam)?

Continuous use of Minoxidil Topical Aerosol 5% (Foam) is needed to maintain hair regrowth.

If you stop using Minoxidil Topical Aerosol 5% (Foam), you will lose your newly regrown hair in 3 to 4 months.

How do I use Men's Minoxidil Topical Aerosol 5% (Foam)?

For best results, apply half a capful 2 times a day directly to the scalp in the hair loss area. Using more than the recommended amount will not improve results. Each can should last one month, if used as directed.

Never take this product by mouth or apply to other parts of the body.

When do I use Men's Minoxidil Topical Aerosol 5% (Foam)?

Apply Minoxidil Topical Aerosol 5% (Foam) once in the morning and once at night. Allow the nighttime application to dry completely before going to bed. Each can should last one month, if used as directed.

What if I miss a dose or forget to use Men's Minoxidil Topical Aerosol 5% (Foam)?

If you miss one or two daily doses of Minoxidil Topical Aerosol 5% (Foam), just continue with your next dose. You should not make up for missed doses.

Can I use Men's Minoxidil Topical Aerosol 5% (Foam) more than twice a day? Will it work faster, better?

No. Minoxidil Topical Aerosol 5% (Foam) will not work faster or better if used more than two times a day. More frequent use or larger doses have not been shown to speed up hair growth and may increase your chance of side effects.

What kind of shampoo should I use with Men's Minoxidil Topical Aerosol 5% (Foam)?

If you wash your scalp before applying Minoxidil Topical Aerosol 5% (Foam), use a mild shampoo.

Can I use hair sprays, mousses, conditioners, gels, etc.?

Yes. Hair sprays, spritz, or styling aids may be used on your hair while using Minoxidil Topical Aerosol 5% (Foam). For best results, Minoxidil Topical Aerosol 5% (Foam) should be allowed to soak into the scalp before using any styling products. Try to develop a good routine of applying Minoxidil Topical Aerosol 5% (Foam) first, and then applying styling products and style as usual. Keep in mind that your best results will be seen with proper application.

Can I have my hair colored or permed or use hair relaxers while using Men's Minoxidil Topical Aerosol 5% (Foam)?

Yes. We have no evidence that coloring or perming your hair or that the use of relaxers change the effect of Minoxidil Topical Aerosol 5% (Foam). However, because the use of a permanent wave and hair color can cause scalp irritation on certain people, we recommend the following precautions:

1. To avoid possible scalp irritation, you should make sure all of the Minoxidil Topical Aerosol 5% (Foam) has been washed off the hair and scalp before using color or perm chemicals.
2. For best results, do not apply Minoxidil Topical Aerosol 5% (Foam) on the same day that you use a chemical treatment on your hair.
3. Do not use Minoxidil Topical Aerosol 5% (Foam) for 24 hours after using any chemicals to make sure your scalp has not been irritated by the perm or color treatment. If no irritation occurs, continue use of Minoxidil Topical Aerosol 5% (Foam) as usual.
4. Simply restart your normal Minoxidil Topical Aerosol 5% (Foam) routine. There is no need to use more Minoxidil Topical Aerosol 5% (Foam) to make up for missed applications.

Missing one day of Minoxidil Topical Aerosol 5% (Foam) will not affect your hair regrowth results.

Can I apply Men's Minoxidil Topical Aerosol 5% (Foam) and wash my hair an hour later?

No. For Minoxidil Topical Aerosol 5% (Foam) to work best, you should allow it to stay on the scalp for about 4 hours before washing.

Using the Product:

- Please familiarize yourself with the instructions below in order to help make your product application a success.
- This product should be used TWICE DAILY, EVERY DAY.
- To be effective, it is important to apply the product DIRECTLY TO YOUR SCALP and NOT TO YOUR HAIR so that it can easily get to your hair follicles to help regrow your hair.
- There is no need to shampoo your hair before using the product. If you wish to shampoo your hair before applying Men's Minoxidil Topical Aerosol 5% (Foam), towel dry your hair so that the skin on the scalp is dry.

1: PREP HANDS WITH COLD WATER
Rinse your fingers in cold water and dry them. Note: foam will melt on contact with warm surfaces.
2: OPEN CHILD RESISTANT CAP
Be sure to align arrow on the cap with arrow on white ring. Tilt cap back and pull off.
3: DISPENSE VERTICALLY ONTO A COLD SURFACE
Hold the can straight upside down. If you hold the can at an angle, foam may not dispense properly. Press nozzle to dispense half a capful of foam onto cold surface (e.g. dish, or cold hands).
4: APPLY TO SCALP, NOT HAIR
Part your hair to expose hair loss area. Massage foam into scalp, not hair. Repeat until all hair loss areas have been covered.
5: CLOSE CAP AND WASH HANDS
Snap cap back into place. Be sure arrows do not line up, so cap remains child resistant. Wash hands and any surface thoroughly after use.

Warnings:

For external use only

For use by men only

Extremely Flammable: Avoid fire, flame, or smoking during and immediately following application.

Do not use if

- you are a woman
- your amount of hair loss is different than that shown on the other side of this leaflet or your hair loss is on the front of the scalp. 5% minoxidil topical foam is not intended for frontal baldness or receding hairline.
- you have no family history of hair loss
- your hair loss is sudden and/or patchy
- you do not know the reason for your hair loss
- you are under 18 years of age. Do not use on babies or children.
- your scalp is red, inflamed, infected, irritated, or painful
- you use other medicines on the scalp

Ask your doctor before use if you have heart disease.

When using this product

- do not apply on other parts of the body
- avoid contact with the eyes. In case of accidental contact, rinse eyes with large amounts of cool tap water.
- contact between children and minoxidil application sites should be avoided. Cases of excessive hair growth have been reported in infants following skin contact with minoxidil application sites of caregivers using topical minoxidil. Excessive hair growth was reversible, within months, when infants were no longer exposed to minoxidil.
- some people may experience changes in hair color and/or texture
- it takes time to regrow hair. Results may occur at 2 months with twice a day usage. For some men, you may need to use this product for at least 4 months before you see results.
- the amount of hair regrowth is different for each person. This product will not work for all men.

Stop use and ask a doctor if

- chest pain, rapid heartbeat, faintness, or dizziness occurs
- sudden, unexplained weight gain occurs
- your hands or feet swell
- scalp irritation or redness occurs
- unwanted facial hair growth occurs
- you do not see hair regrowth in 4 months

Not for use by women.

May be harmful if used when pregnant or breast-feeding.

Keep out of reach of children and pets. If swallowed, get medical help or contact a poison control center (1-800-222-1222) right away.

What are the most common side effects with Men's Minoxidil Topical Aerosol 5% (Foam)?

The most common side effects are itching and skin irritation of the treated area of the scalp. If scalp irritation continues, stop use and see a doctor. Minoxidil Topical Aerosol 5% (Foam) contains alcohol, which will cause burning or irritation of the eyes. If Minoxidil Topical Aerosol 5% (Foam) accidentally gets into eyes, rinse with large amounts of cool tap water.

Can Men's Minoxidil Topical Aerosol 5% (Foam) produce unwanted hair growth?

Unwanted hair growth on the face and other parts of the body has been reported in women. But it is rare and reversible. If you develop unwanted hair, stop using Minoxidil Topical Aerosol 5% (Foam). Over time, the unwanted hair growth caused by Minoxidil Topical Aerosol 5% (Foam) will go away. You can take the following steps to decrease the chances of unwanted hair growth:

1. limit the application of Minoxidil Topical Aerosol 5% (Foam) only to the scalp;
2. if you use your hands to apply Minoxidil Topical Aerosol 5% (Foam), wash your hands well immediately afterwards.

Can I use Men's Minoxidil Topical Aerosol 5% (Foam) for baldness or hair loss in babies or children?

No. Minoxidil Topical Aerosol 5% (Foam) must not be used to treat baldness or hair loss in babies and children.

If you have any other questions, ask your health care professional or call us at 1-855-274-4122 (Monday – Friday 8:30 AM to 5:00 PM EST).

Store at 20° to 25°C (68° to 77°F) [See USP Controlled Room Temperature]. Contents under pressure. Do not puncture or incinerate container. Do not expose to heat or store at temperatures above 120°F (49°C).

Save this leaflet for future reference.

• To Open:

1. Be sure to align arrow on the cap with arrow on white ring.
2. Tilt cap back and pull off.

• To Close:

1. Place CAP on container and snap into place.
2. Be sure arrows DO NOT line up so CAP remains child resistant.

Distributed by:
AUROHEALTH LLC
279 Princeton-Hightstown Road
East Windsor, NJ 08520

Questions? call toll-free 1-855-274-4122 (Monday – Friday 8:30 AM to 5:00 PM EST).
Revised: 01/2026

PRINCIPAL DISPLAY PANEL - One 60 g Can Label

FOR BEST RESULTS
USE TWICE DAILY
APPLY DIRECTLY TO SCALP

Minoxidil
Topical
Aerosol 5%
(For Men)
HAIR REGROWTH
TREATMENT
REACTIVATES
HAIR FOLLICLES
TO STIMULATE REGROWTH
EASY-TO-USE FOAM
UNSCENTED

Not For Use By Women

One Month Supply
One 60 g (2.11 oz) Can

PRINCIPAL DISPLAY PANEL - One 60 g Can Carton

AUROHEALTH
NDC 58602-608-01

*Compare to the active ingredient
of Men's Rogaine®

Minoxidil Topical
Aerosol 5%
(For Men)

HAIR REGROWTH
TREATMENT

REACTIVATES
HAIR FOLLICLES
TO STIMULATE REGROWTH

EASY-TO-USE
FOAM

CLINICALLY PROVEN TO
HELP REGROW HAIR

UNSCENTED

Not For Use By Women

One Month Supply
• One 60 g (2.11 oz) Can